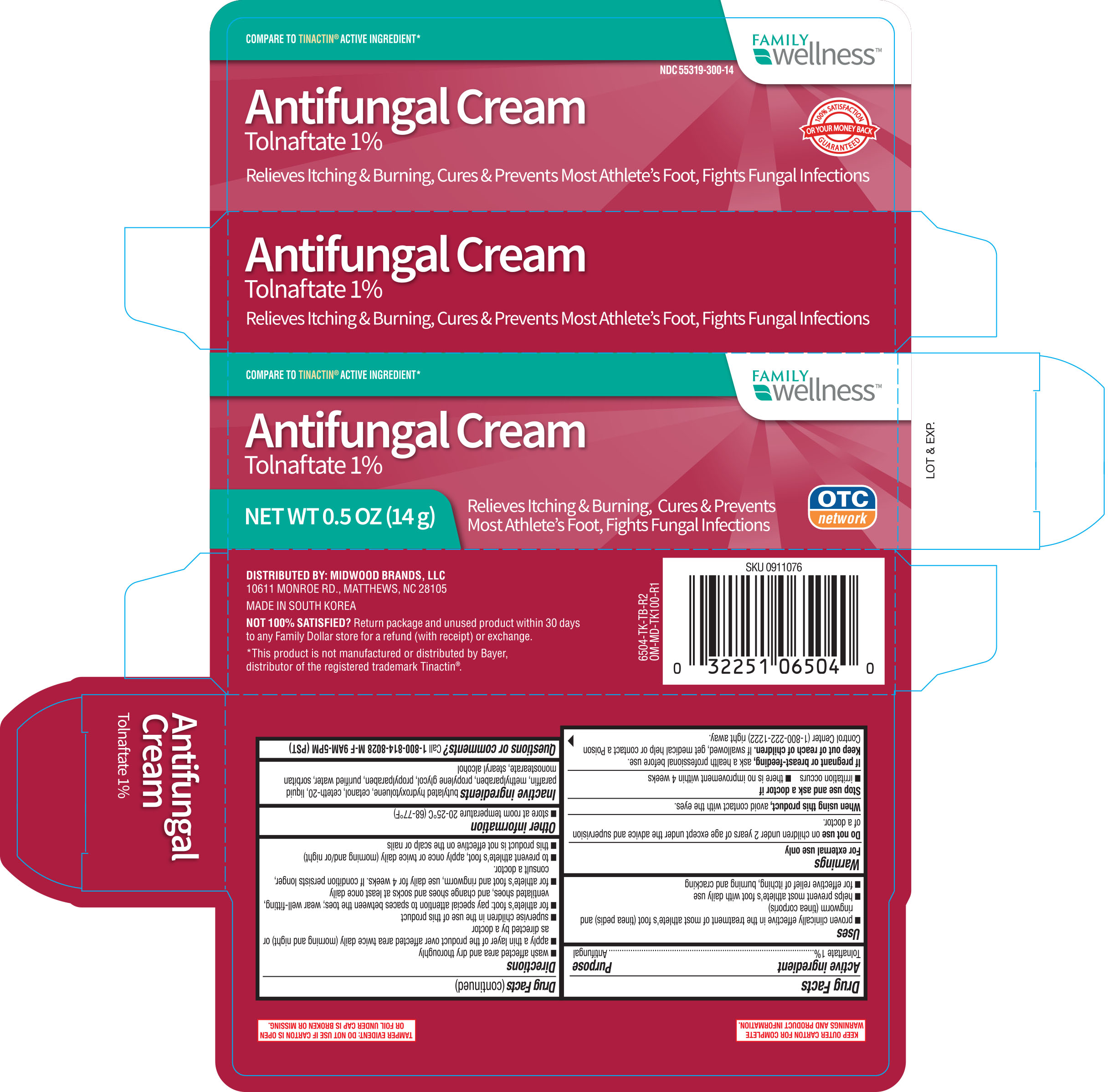 DRUG LABEL: Family Wellness Antifungal
NDC: 55319-300 | Form: CREAM
Manufacturer: Family Dollar
Category: otc | Type: HUMAN OTC DRUG LABEL
Date: 20190312

ACTIVE INGREDIENTS: TOLNAFTATE 1 g/100 g
INACTIVE INGREDIENTS: CETETH-20; CETYL ALCOHOL; METHYLPARABEN; PARAFFIN; SORBITAN MONOSTEARATE; PROPYLENE GLYCOL; WATER; STEARYL ALCOHOL; BUTYLATED HYDROXYTOLUENE

Family Wellness Anti-Fungal Cream Tolnaftate 1% 0.5 oz (6504, 2019)

Active Ingredient Purpose

Tolnaftate 1%................................................ Antifungal

Uses

- proven clinically effective in the treatment of most athlete's foot (tinea pedis) and ringworm (tinea corporis)
- helps prevent most athlete's foot with daily use
- for effective relief of itching, burning, and cracking

Warnings

For external use only

Do not use on children under 2 years of age except under the advice and supervision of a doctor

When using this product avoid contact with the eyes

Stop use and ask a doctor if

- irritation occurs
- there is no improvement within 4 weeks

Keep out of reach of children. If swallowed, get medical help or contact a Poision Control Center right away.

Directions

- wash affected area and dry thoroughly
- apply a thin layer over affected area twice daily (morning and night)
- supervise children in the use of this product
- for athlete's foot: pay special attention to spaces between the toes; wear well-fitting, ventilated shoes and change shoes and socks at least once daily
- for athlete's foot and ringworm, use daily for 4 weeks. If conditions persist longer, consult a doctor.
- to prevent athlete's foot, apply once or twice daily (morning and/or night)
- this product is not effective on the scalp or nails

Other information

- store at room temperature 20-25°C (68-77°F)

Inactive ingredients

butylated hydroxytoluene, cetanol, ceteth-20, liquid paraffin, methylparaben, propylene glycol, propylparaben, purified water, sorbitan, monostearate, stearyl alcohol

DOSAGE AND ADMINISTRATION

DISTRIBUTED BY:

10611 MONOROE RD., MATTHEWS, NC 28105

MADE IN SOUTH KOREA